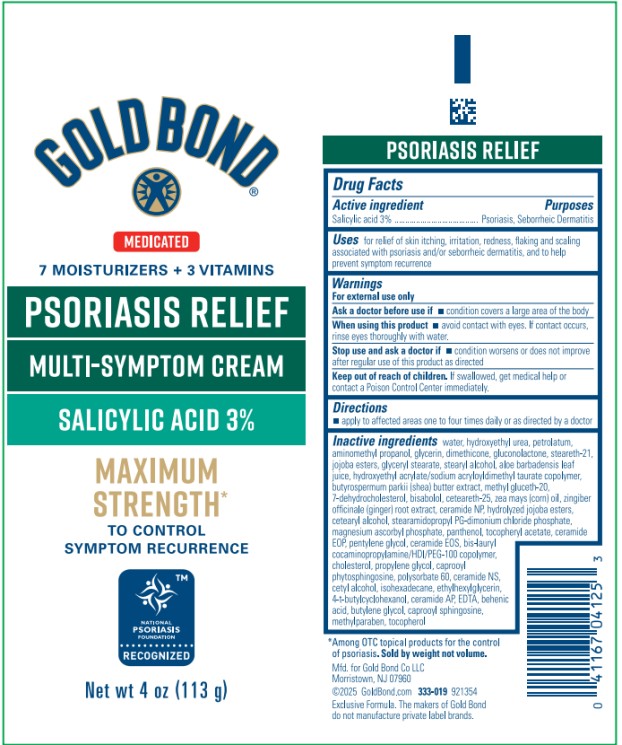 DRUG LABEL: Gold Bond Psoriasis Relief Medicated Multi-Symptom
NDC: 84714-0413 | Form: CREAM
Manufacturer: Gold Bond Co LLC
Category: otc | Type: HUMAN OTC DRUG LABEL
Date: 20251204

ACTIVE INGREDIENTS: SALICYLIC ACID 3 g/100 g
INACTIVE INGREDIENTS: WATER; HYDROXYETHYL UREA; PETROLATUM; AMINOMETHYLPROPANOL; GLYCERIN; DIMETHICONE; GLUCONOLACTONE; STEARETH-21; HYDROGENATED JOJOBA OIL, RANDOMIZED; GLYCERYL STEARATE; STEARYL ALCOHOL; ALOE VERA LEAF; HYDROXYETHYL ACRYLATE/SODIUM ACRYLOYLDIMETHYL TAURATE COPOLYMER (45000 MPA.S AT 1%); SHEA BUTTER; METHYL GLUCETH-20; 7-DEHYDROCHOLESTEROL; LEVOMENOL; CETEARETH-25; CORN OIL; GINGER; CERAMIDE NP; HYDROLYZED JOJOBA ESTERS (ACID FORM); CETEARYL ALCOHOL; STEARAMIDOPROPYL PG-DIMONIUM CHLORIDE PHOSPHATE; MAGNESIUM ASCORBYL PHOSPHATE; PANTHENOL; ALPHA-TOCOPHEROL ACETATE; PENTYLENE GLYCOL; CERAMIDE EOS; CHOLESTEROL; PROPYLENE GLYCOL; CAPROOYL PHYTOSPHINGOSINE; POLYSORBATE 60; CERAMIDE NS; CETYL ALCOHOL; ISOHEXADECANE; ETHYLHEXYLGLYCERIN; 4-T-BUTYLCYCLOHEXANOL; CERAMIDE AP; EDTA; BEHENIC ACID; BUTYLENE GLYCOL; CAPROOYL SPHINGOSINE; METHYLPARABEN; TOCOPHEROL

Gold Bond Psoriasis Relief Cream

Gold Bond Psoriasis Relief Medicated Multi-Symptom Cream

Drug Facts

Active ingredient

Salicylic acid 3%

Purposes

Psoriasis, Seborrheic Dermatitis

Uses

For relief of skin itching, irritation, redness, flaking and scaling associated with psoriasis and/or seborrheic dermatitis, and to help prevent symptom recurrence

Warnings

For external use only

Ask a doctor before use if

- condition covers a large area of the body

When using this product

- avoid contact with the eyes. If contact occurs, rinse eyes thoroughly with water.

Stop use and ask a doctor if

- condition worsens or does not improve after regular use of this product as directed

Keep out of reach of children.

If swallowed, get medical help or contact a Poison Control Center immediately.

Directions

Apply to affected areas one to four times daily or as directed by a doctor

Inactive ingredients

water, hydroxyethyl urea, petrolatum, aminomethyl propanol, glycerin, dimethicone, gluconolactone, steareth-21, jojoba esters, glyceryl stearate, stearyl alcohol, aloe barbadensis leaf juice, hydroxyethyl acrylate/sodium acryloyldimethyl taurate copolymer, butyrospermum parkii (shea) butter extract, methyl gluceth-20, 7-dehydrocholesterol, bisabolol, ceteareth-25, zea mays (corn) oil, zingiber officinale (ginger) root extract, ceramide NP, hydrolyzed jojoba esters, cetearyl alcohol, stearamidopropyl PG-dimonium chloride phosphate, magnesium ascorbyl phosphate, panthenol, tocopheryl acetate, ceramide EOP, pentylene glycol, ceramide EOS, bis-lauryl cocaminopropylamine/HDI/PEG-100 copolymer, cholesterol, propylene glycol, caprooyl phytosphingosine, polysorbate 60, ceramide NS, cetyl alcohol, isohexadecane, ethylhexylglycerin, 4-t-butylcyclohexanol, ceramide AP, EDTA, behenic acid, butylene glycol, caprooyl sphingosine, methylparaben, tocopherol

PRINCIPAL DISPLAY PANEL

Gold Bond Psoriasis Relief Medicated Multi-Symptom Cream
Net wt 4 oz (113 g)